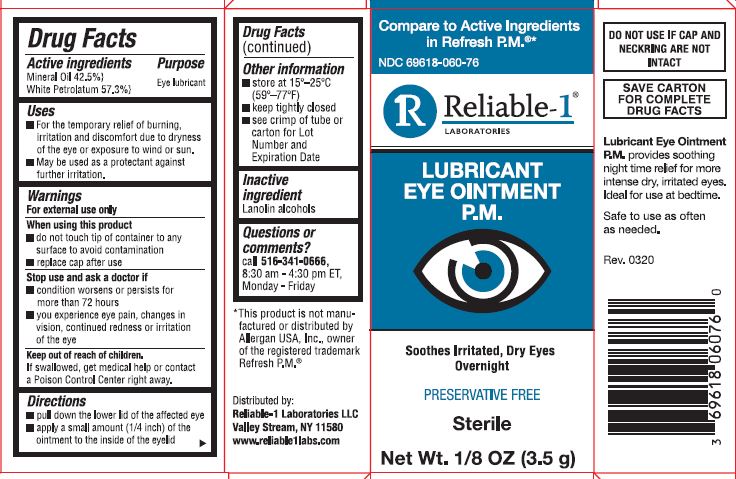 DRUG LABEL: Lubricant Eye PM
NDC: 69618-060 | Form: OINTMENT
Manufacturer: Reliable 1 Laboratories LLC
Category: otc | Type: HUMAN OTC DRUG LABEL
Date: 20241231

ACTIVE INGREDIENTS: MINERAL OIL 42.5 g/100 g; WHITE PETROLATUM 57.3 g/100 g
INACTIVE INGREDIENTS: LANOLIN ALCOHOLS

Lubricant Eye Ointment P.M.

Drug Facts

Active ingredients

Mineral Oil 42.5%

White Petrolatum 57.3%

Purpose

Eye lubricant

Uses

- For the temporary relief of burning, irritation and discomfort due to dryness of the eye or exposure to wind or sun.
- May be used as a protectant against further irritation.

Warnings

For external use only

When using this product

- do not touch tip of container to any surface to avoid contamination
- replace cap after use

Stop use and ask a doctor if

- condition worsens or persists for more than 72 hours
- you experience eye pain, changes in vision, continued redness or irritation of the eye

Keep out of reach of children. If swallowed, get medical help or contact a Poison Control Center right away.

Directions

- pull down the lower lid of the affected eye
- apply a small amount (1/4 inch) of the ointment to the inside of the eyelid

Other information

- store at 15°-25°C (59°-77°F)
- keep tightly closed
- see crimp of tube or carton for Lot Number and Expiration Date

Inactive ingredient

Lanolin alcohols

Questions or comments?

call 516-341-0666, 8:30 - 4:30 pm ET, Monday - Friday

*This product is not manufactured or distributed by Allergan USA, Inc., owner of the registered trademark Refresh P.M.

Distributed by:

Reliable-1 Laboratories LLC

Valley Stream, NY 11580

www.reliable1labs.com

DO NOT USE IF CAP AND NECKRING ARE NOT INTACT

SAVE CARTON FOR COMPLETE DRUG FACTS

Lubricant Eye Ointment P.M. provides soothing night time relief for more intense dry, irritated eyes. Ideal for use at bedtime.

Safe to use as often as needed.

PACKAGE LABEL

Compare to Active Ingredients in Refresh P.M.®*

NDC 69618-060-76

Reliable-1® LABORATORIES

LUBRICANT EYE OINTMENT P.M.

Soothes Irritated, Dry Eyes Overnight

PRESERVATIVE FREE

Sterile

Net Wt. 1/8 OZ (3.5 g)